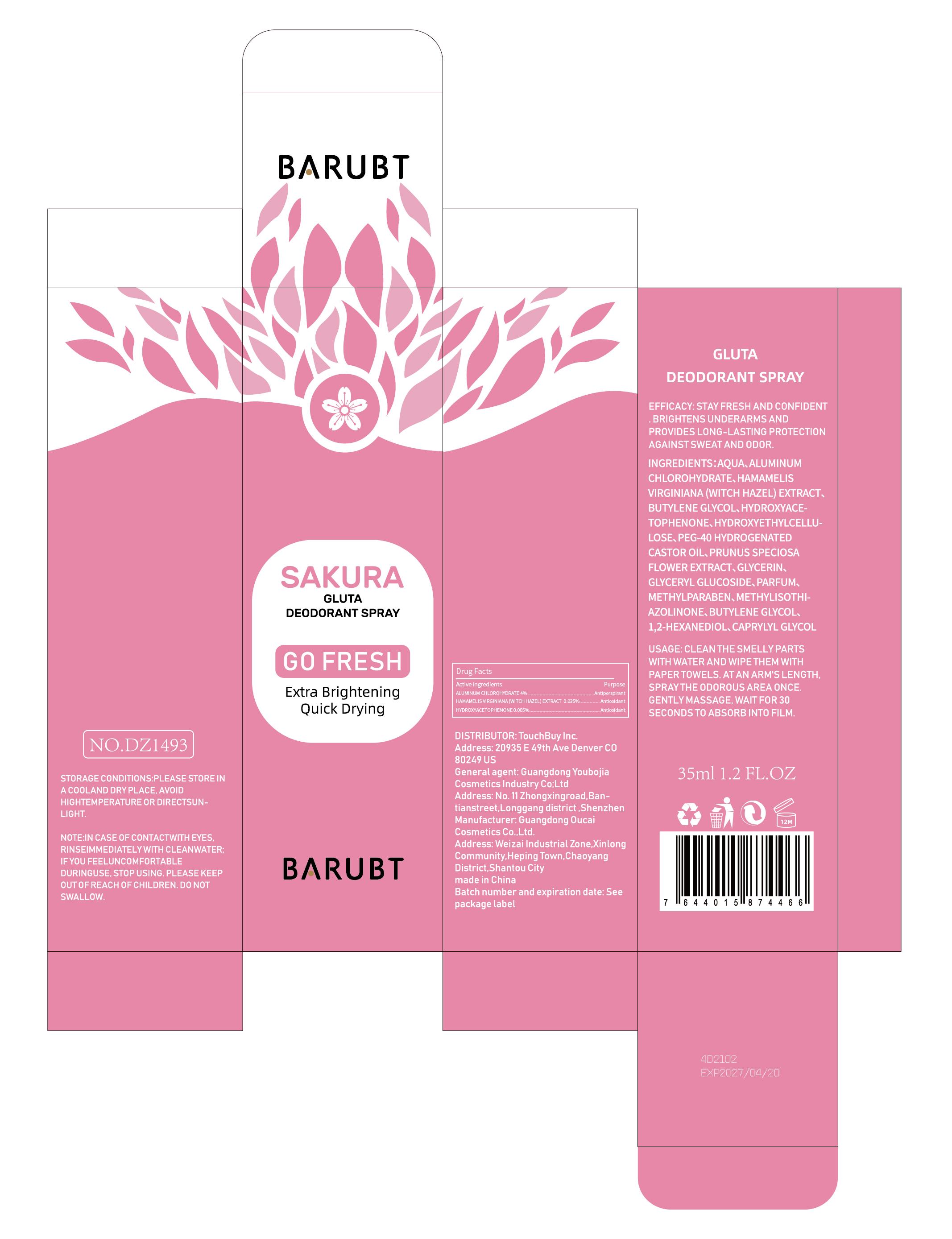 DRUG LABEL: BARUBT Gluta Deodorant Spary
NDC: 84712-012 | Form: SPRAY
Manufacturer: Guangdong Youbaijia Cosmetic Industry Co., Ltd
Category: otc | Type: HUMAN OTC DRUG LABEL
Date: 20240914

ACTIVE INGREDIENTS: ALUMINUM CHLOROHYDRATE 1.4 g/35 mL; HAMAMELIS VIRGINIANA WHOLE 0.01225 g/35 mL; HYDROXYACETOPHENONE 0.00175 g/35 mL
INACTIVE INGREDIENTS: BUTYLENE GLYCOL 0.0105 g/35 mL

ACTIVE INGREDIENT

ALUMINUM CHLOROHYDRATE 4%
HAMAMELIS VIRGINIANA(WITCH HAZEL)EXTRACT 0.035%
HYDROXYACETOPHENONE 0.005%

INACTIVE INGREDIENT

AQUA
BUTYLENE GLYCOL
HYDROXYETHYLCELLULOSE
PEG-40 HYDROGENATED CASTOR OIL
PRUNUS SPECIOSA FLOWER EXTRACT
GLYCERIN
GLYCERYL GLUCOSIDE
PARFUM
METHYLPARABEN
METHYLISOTHIAZOLINONE
BUTYLENE GLYCOL
1,2-HEXANEDIOL
CAPRYLYL GLYCOL

Do not use on damaged skin.

Keep away from children. Do not swallow.

PURPOSE

DEODORANT

QUESTIONS

Contact name: Jessie Peng
Company phone number: +1 818 579 7288
Company e-mail: jessie@registeragentllc.com

STOP USE

lf skin becomes red or irritated, discontinue use immediately and wash with water.

WHEN USING

keep out of eyes. Rinse with water to remove.

STORAGE AND HANDLING

Keep away from light and in adry place.

INDICATIONS AND USAGE

STAY FRESH AND CONFIDENT BRIGHTENS UNDERARMS AND PROVIDES LONG-LASTING PROTECTION AGAINSTSWEAT AND ODOR.

WARNINGS

For external use only.

DOSAGE AND ADMINISTRATION

CLEAN THE SMELLYPARTS WITH WATER AND WIPETHEM WITH PAPERTOWELS.AT AN ARM'S LENGTH,SPRAY THE ODOROUS AREA ONCE.GENTLY MASSAGE.WAIT FOR 30 SECONDS TO ABSORB INTO FILM.